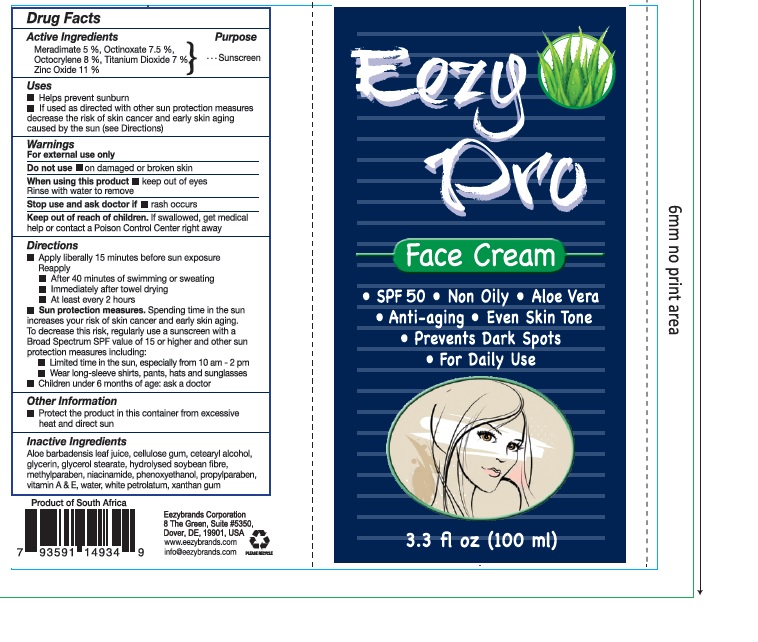 DRUG LABEL: Eezy pro
NDC: 70116-010 | Form: CREAM
Manufacturer: BIO EARTH MANUFACTURING (PTY) LTD
Category: otc | Type: HUMAN OTC DRUG LABEL
Date: 20241024

ACTIVE INGREDIENTS: MERADIMATE 5 mg/100 mL; OCTINOXATE 7.5 mg/100 mL; OCTOCRYLENE 8 mg/100 mL; TITANIUM DIOXIDE 7 mg/100 mL; ZINC OXIDE 11 mg/100 mL
INACTIVE INGREDIENTS: BULBINE FRUTESCENS WHOLE; CARBOXYMETHYLCELLULOSE SODIUM, UNSPECIFIED FORM; CETOSTEARYL ALCOHOL; GLYCERIN; GLYCERYL MONOSTEARATE; NIACINAMIDE; METHYLPARABEN; PHENOXYETHANOL; PROPYLPARABEN; .ALPHA.-TOCOPHEROL; WATER; VITAMIN A; PETROLATUM; XANTHAN GUM; HYDROLYZED SOY PROTEIN (ENZYMATIC; 2000 MW)

Eezy pro

Active Ingredient

Meradimate, Octinoxate, Octocrylene, Titanium Dioxide, Zinc Oxide

Purpose

Sunscreen

Uses

•Helps prevent sunburn
•If used as directed with other sun protection measures decreases the risk of skin cancer and early skin aging caused by sun(see Directions)

Warnings

For external use only.

Do not use on damaged or broken skin

When using this product keep out of eyes. Rinse with water to remove.

Stop use and ask a doctor if rash occurs.

Keep out of reach of children

If swallowed, get medical help or contact a Poison Control Center right away.

Directions

•Apply liberally 15 minutes before sun exposure

Reapply
•After 40 minutes of swimming or sweating

•Immediately after towel drying

•At least every 2 hours.

• Sun Protection Measures.

Spending time in the sun increases your risk of skin cancer and early skin aging.

To decrease this risk, regularly use a sunscreen with a Broad Spectrum SPF value of 15 or higher and other sun protection measures including:

•Limited time in the sun, espesially from 10 a.m - 2 p.m

•Wear long-sleeved shirts, pants, hats and sunglasses

• Children under 6 months of age: ask a doctor

Inactive Ingredient

Aloe barbadensis leaf juice, Cellulose gum, Cetearyl alcohol, Glycerin, Glycerol Stearate, Methylparaben, Phenoxyethanol, Propylparaben,

Vitamin A & E, Water, White petrolatum, Xanthan gum,Niacinamide,hydrolysed soybean fibre.

Other Information

Protect the product in this container from excessive heat and direct sun.